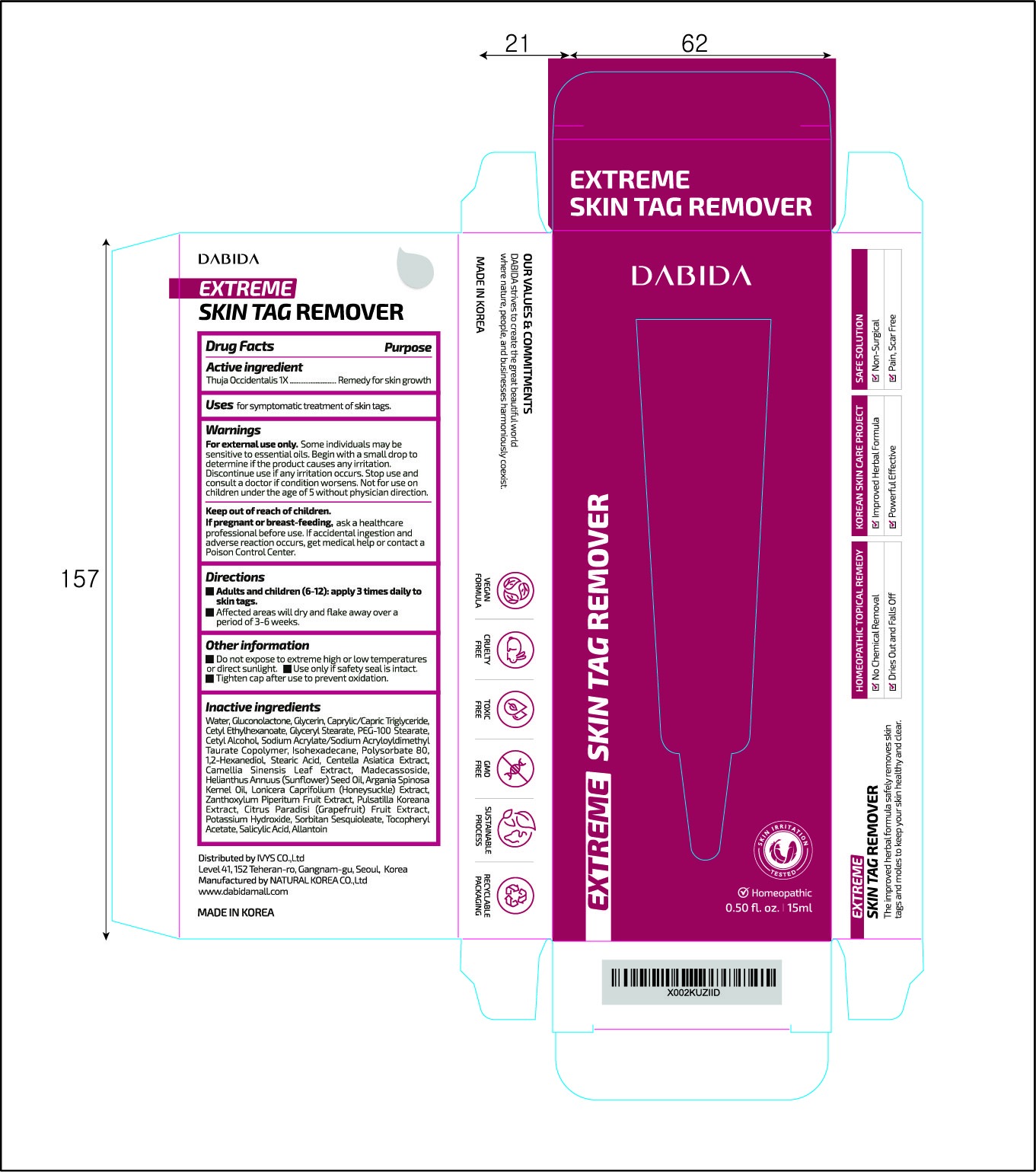 DRUG LABEL: DABIDA EXTREME SKIN TAG REMOVER
NDC: 74646-0016 | Form: CREAM
Manufacturer: Natural Korea Co., Ltd.
Category: homeopathic | Type: HUMAN OTC DRUG LABEL
Date: 20201027

ACTIVE INGREDIENTS: THUJA OCCIDENTALIS LEAF 1 [hp_X]/15 mL
INACTIVE INGREDIENTS: POLYSORBATE 80; GREEN TEA LEAF; ARGAN OIL; LONICERA CAPRIFOLIUM FLOWER; SORBITAN SESQUIOLEATE; .ALPHA.-TOCOPHEROL ACETATE; SODIUM ACRYLATE/SODIUM ACRYLOYLDIMETHYLTAURATE COPOLYMER (4000000 MW); GLUCONOLACTONE; GLYCERIN; MEDIUM-CHAIN TRIGLYCERIDES; WATER; GLYCERYL MONOSTEARATE; PEG-100 STEARATE; CETYL ALCOHOL; CETYL ETHYLHEXANOATE; PULSATILLA KOREANA WHOLE; ISOHEXADECANE; 1,2-HEXANEDIOL; STEARIC ACID; CENTELLA ASIATICA; MADECASSOSIDE; SUNFLOWER OIL; ZANTHOXYLUM PIPERITUM FRUIT PULP; GRAPEFRUIT; POTASSIUM HYDROXIDE; SALICYLIC ACID; TEA TREE OIL; ALLANTOIN

[OTC-HOMEOPHATIC]
DABIDA EXTREME SKIN TAG REMOVER: 74646-0016-1